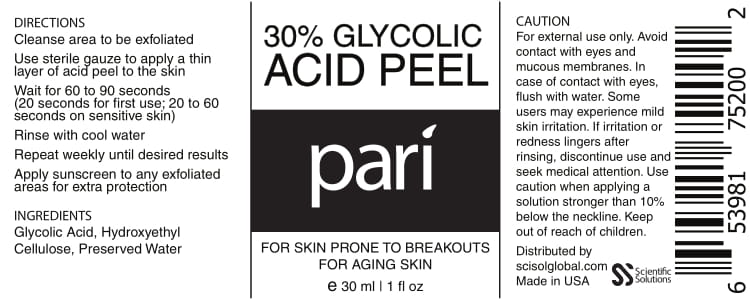 DRUG LABEL: Glycolic Acid
NDC: 81376-701 | Form: LIQUID
Manufacturer: SSG Ventures Inc
Category: otc | Type: HUMAN OTC DRUG LABEL
Date: 20210407

ACTIVE INGREDIENTS: GLYCOLIC ACID 9 g/30 mL
INACTIVE INGREDIENTS: WATER; HYDROXYETHYL CELLULOSE (100 MPA.S AT 2%)

pari Glycolic Acid Peel

PACKAGE LABEL

INGREDIENTS

Glycolic Acid

PURPOSE

FOR SKIN PRONE TO BREAKOUTS
FOR AGING SKIN

Keep out of reach of children.

WARNINGS

CAUTION
For external use only. Avoid contact with eyes and\ mucous membranes. In case of contact with eyes, flush with water. Some users may experience mild skin irritation. If irritation or redness lingers after rinsing, discontinue use and seek medical attention. Use caution when applying a solution stronger than 10% below the neckline. Keep out of reach of children.

PURPOSE

FOR SKIN PRONE TO BREAKOUTS
FOR AGING SKIN

DIRECTIONS
Cleanse area to be exfoliated

Use sterile gauze to apply a thin layer of acid peel to the skin

Wait for 60 to 90 seconds (20 seconds for first use; 20 to 60 seconds on sensitive skin)

Rinse with cool water

Repeat weekly until desired results

Apply sunscreen to any exfoliated areas for extra protection

INACTIVE INGREDIENT

Hydroxyethyl Cellulose, Preserved Water

DOSAGE AND ADMINISTRATION

Cleanse area to be exfoliated

Use sterile gauze to apply a thin layer of acid peel to the skin

Wait for 60 to 90 seconds (20 seconds for first use; 20 to 60 seconds on sensitive skin)

Rinse with cool water

Repeat weekly until desired results

Apply sunscreen to any exfoliated areas for extra protection

INDICATIONS AND USAGE

FOR SKIN PRONE TO BREAKOUTS
FOR AGING SKIN